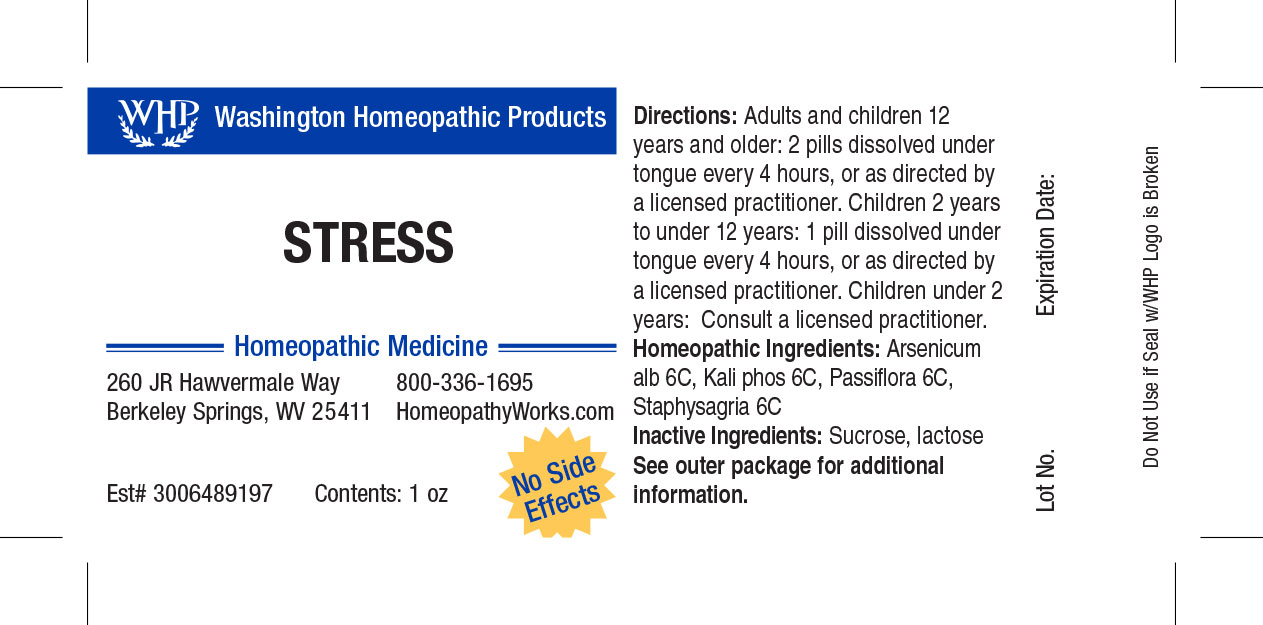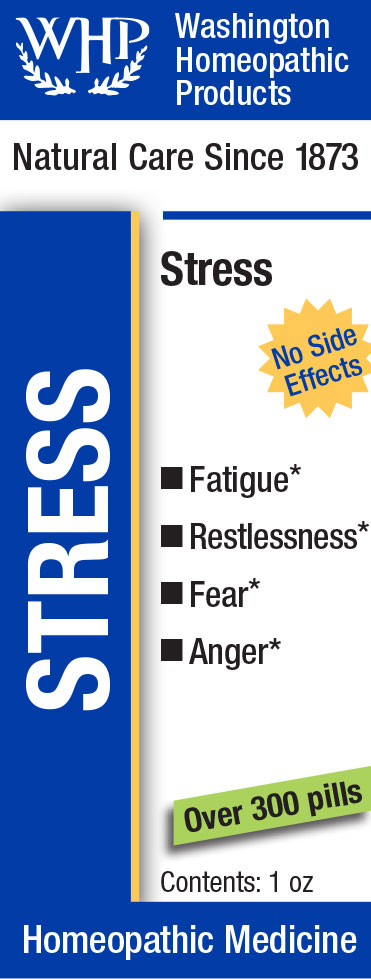 DRUG LABEL: WHP Stress
NDC: 71919-809 | Form: PELLET
Manufacturer: Washington Homeopathic Products
Category: homeopathic | Type: HUMAN OTC DRUG LABEL
Date: 20250128

ACTIVE INGREDIENTS: DELPHINIUM STAPHISAGRIA SEED 6 [hp_C]/1 1; POTASSIUM PHOSPHATE, DIBASIC 6 [hp_C]/1 1; PASSIFLORA INCARNATA FLOWERING TOP 6 [hp_C]/1 1; ARSENIC TRIOXIDE 6 [hp_C]/1 1
INACTIVE INGREDIENTS: LACTOSE; SUCROSE

WHP Stress

ACTIVE INGREDIENTS

ARSENICUM ALB 6C

KALI PHOS 6C

PASSIFLORA 6C

STAPHYSAG 6C

USES

Temporarily relieves fear and worrying often brought on by stress.

INDICATIONS

ARSENICUM ALB Vomiting

KALI PHOS Irritability

PASSIFLORA Sleeplessness

STAPHYSAG Anger

STOP USE AND ASK DOCTOR

If symptoms persist or recur, discontinue use. If pregnant or nursing, consult a licensed practitioner before using this product.

DIRECTIONS

Directions: Adults and children 12 years and older: 2 pills dissolved under tongue every 4 hours, or as directed by a licensed practitioner. Children 4 years to under 12 years: 1 pill dissolved under tongue every 4 hours, or as directed by a licensed practitioner. Children under 4 years: Consult a licensed practitioner.

INACTIVE INGREDIENTS

Sucrose/Lactose

KEEP OUT OF REACH OF CHILDREN

As with all medications, keep out of reach of children.